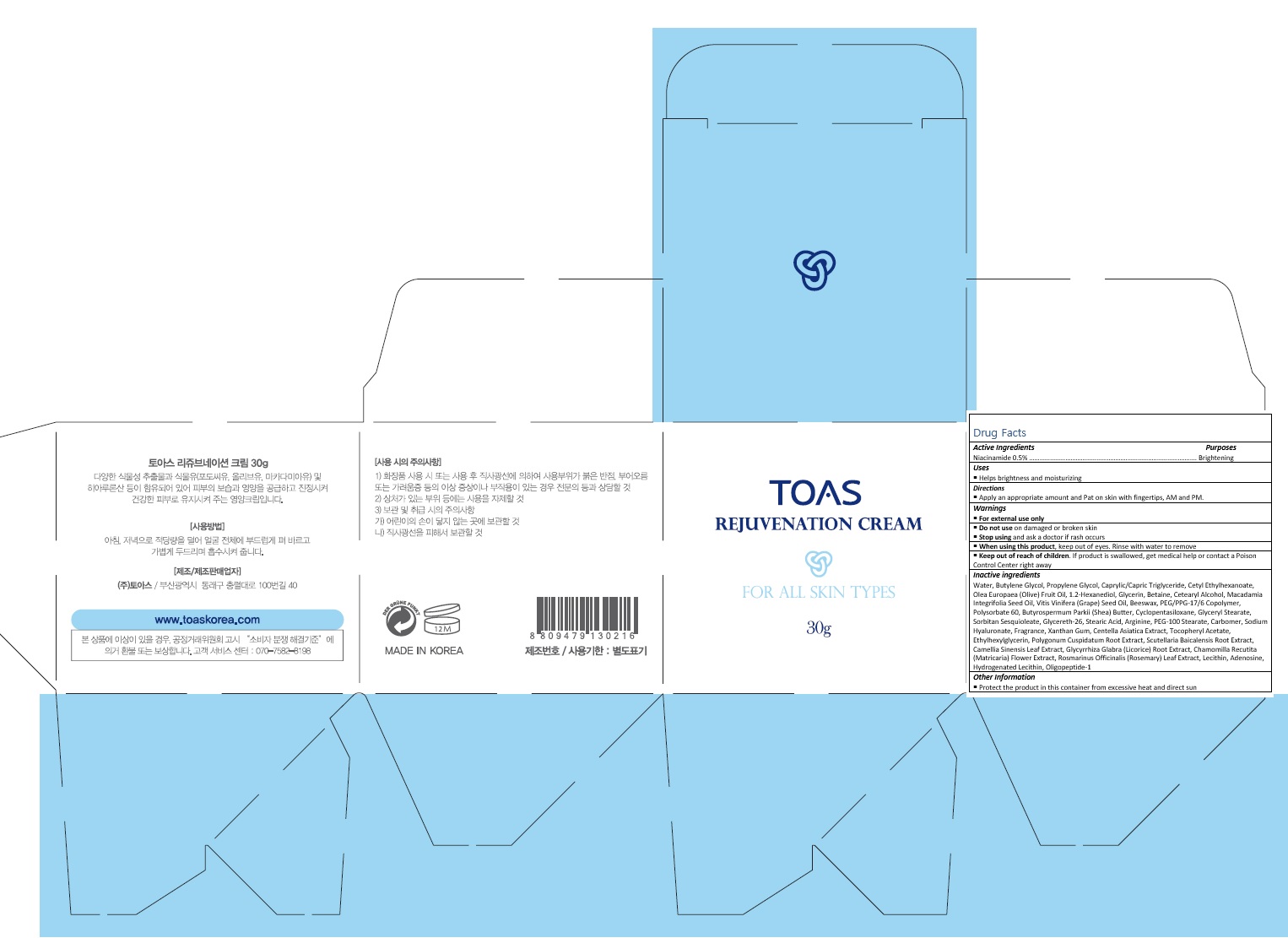 DRUG LABEL: TOAS Rejuvenation
NDC: 72557-004 | Form: CREAM
Manufacturer: TOAS Co., Ltd.
Category: otc | Type: HUMAN OTC DRUG LABEL
Date: 20180924

ACTIVE INGREDIENTS: NIACINAMIDE 0.15 g/30 g
INACTIVE INGREDIENTS: WATER; BUTYLENE GLYCOL; MEDIUM-CHAIN TRIGLYCERIDES; CETYL ETHYLHEXANOATE; OLIVE OIL; 1,2-HEXANEDIOL; GLYCERIN; BETAINE; CETOSTEARYL ALCOHOL; GRAPE SEED OIL; PEG/PPG-17/6 COPOLYMER; POLYSORBATE 60; SHEA BUTTER; CYCLOMETHICONE 5; GLYCERYL MONOSTEARATE

72557-004_TOAS Rejuvenation

ACTIVE INGREDIENT

Niacinamide 0.5%

PURPOSE

Brightening

INDICATIONS AND USAGE

Helps brightness and moisturizing

DOSAGE AND ADMINISTRATION

Apply an appropriate amount and Pat on skin with fingertips, AM and PM.

WARNINGS

For external use only.
Do not use on damaged or broken skin.
When using this product, keep out of eyes. Rinse with water to remove.
Stop using and ask a doctor if rash occurs.

KEEP OUT OF REACH OF CHILDREN

Keep out of reach of the children. If product is swallowed, get medical help or contact a poison control center right away.

INACTIVE INGREDIENT

Water, Butylene Glycol, Propylene Glycol, Caprylic/Capric Triglyceride, Cetyl Ethylhexanoate, Olea Europaea (Olive) Fruit Oil, 1.2-Hexanediol, Glycerin, Betaine, Cetearyl Alcohol, Macadamia Integrifolia Seed Oil, Vitis Vinifera (Grape) Seed Oil, Beeswax, PEG/PPG-17/6 Copolymer, Polysorbate 60, Butyrospermum Parkii (Shea) Butter, Cyclopentasiloxane, Glyceryl Stearate, Sorbitan Sesquioleate, Glycereth-26, Stearic Acid, Arginine, PEG-100 Stearate, Carbomer, Sodium Hyaluronate, Fragrance, Xanthan Gum, Centella Asiatica Extract, Tocopheryl Acetate, Ethylhexylglycerin, Polygonum Cuspidatum Root Extract, Scutellaria Baicalensis Root Extract, Camellia Sinensis Leaf Extract, Glycyrrhiza Glabra (Licorice) Root Extract, Chamomilla Recutita (Matricaria) Flower Extract, Rosmarinus Officinalis (Rosemary) Leaf Extract, Lecithin, Adenosine, Hydrogenated Lecithin, Oligopeptide-1